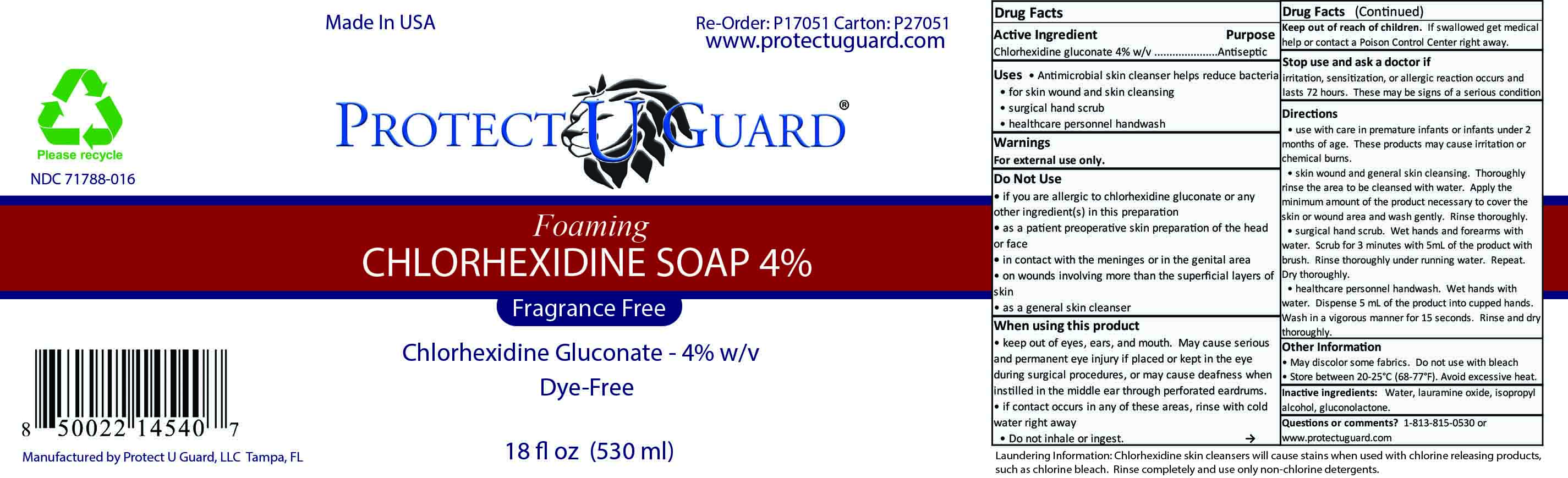 DRUG LABEL: Foaming Chlorhexidine Gluconate
NDC: 71788-016 | Form: LIQUID
Manufacturer: Protect U Guard, LLC
Category: otc | Type: HUMAN OTC DRUG LABEL
Date: 20210412

ACTIVE INGREDIENTS: CHLORHEXIDINE GLUCONATE 4 g/100 mL
INACTIVE INGREDIENTS: WATER; LAURAMINE OXIDE; ISOPROPYL ALCOHOL; GLUCONOLACTONE

Active Ingredient

Chlorhexidine gluconate 4% w/v

Purpose

Antiseptic

Uses

Antimicrobial skin cleanser helps reduce bacteria

for skin wound and skin cleansing

surgical hand scrub

healthcare personnel handwash

Warnings

For external use only.

Do Not Use

if you are allergic to chlorhexidine gluconate or any other ingredient(s) in this preparation

as a patient preoperative skin preparation of the head or face

in contact with the meninges or in the genital area

on wounds involving more than the superficial layers of skin

as a general skin cleanser

When using this product

keep out of eyes, ears, and mouth. May cause serious and permanent eye injury if placed or kept in the eye during surgical procedures, or may cause deafness when instilled in the middle ear through perforated eardrums.

if contact occurs in any of these areas, rinse with cold water right away

do not inhale or ingest

Keep out of reach of children

If swallowed get medical help or contact a Poison Control Center right away.

Stop use and ask a doctor if

irritation, sensitization, or allergic reaction occurs and lasts 72 hours. These may be signs of a serious condition.

Directions

use with care in premature infants under 2 months of age. These products may cause irritation or chemical burns.

skin wound and skin cleansing. Thoroughly rinse the area to be cleansed with water. Apply the minimum amount of the product necessary to cover the skin or wound area and wash gently. Rinse thoroughly

surgical hand scrub. Wet hands and forearms with water. Scrub for 3 minutes with 5mL of the product with brush. Rinse thoroughly under running water. Repeat. Dry thoroughly.

healthcare personnel handwash. Wet hands with water. Dispense 5 mL of the product into cupped hands. Wash in a vigorous manner for 15 seconds. Rinse and dry thoroughly.

Other Information

May discolor some fabrics. Do not use with bleach.

Store between 20-25° C (68-77° F). Avoid excessive heat.

Inactive ingredients:

Water, lauramine oxide, isopropyl alcohol, gluconolactone.

Questions or comments?

1-813-815-0530 or www.protectuguard.com